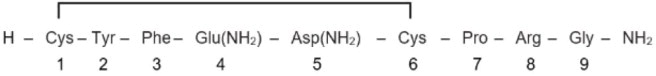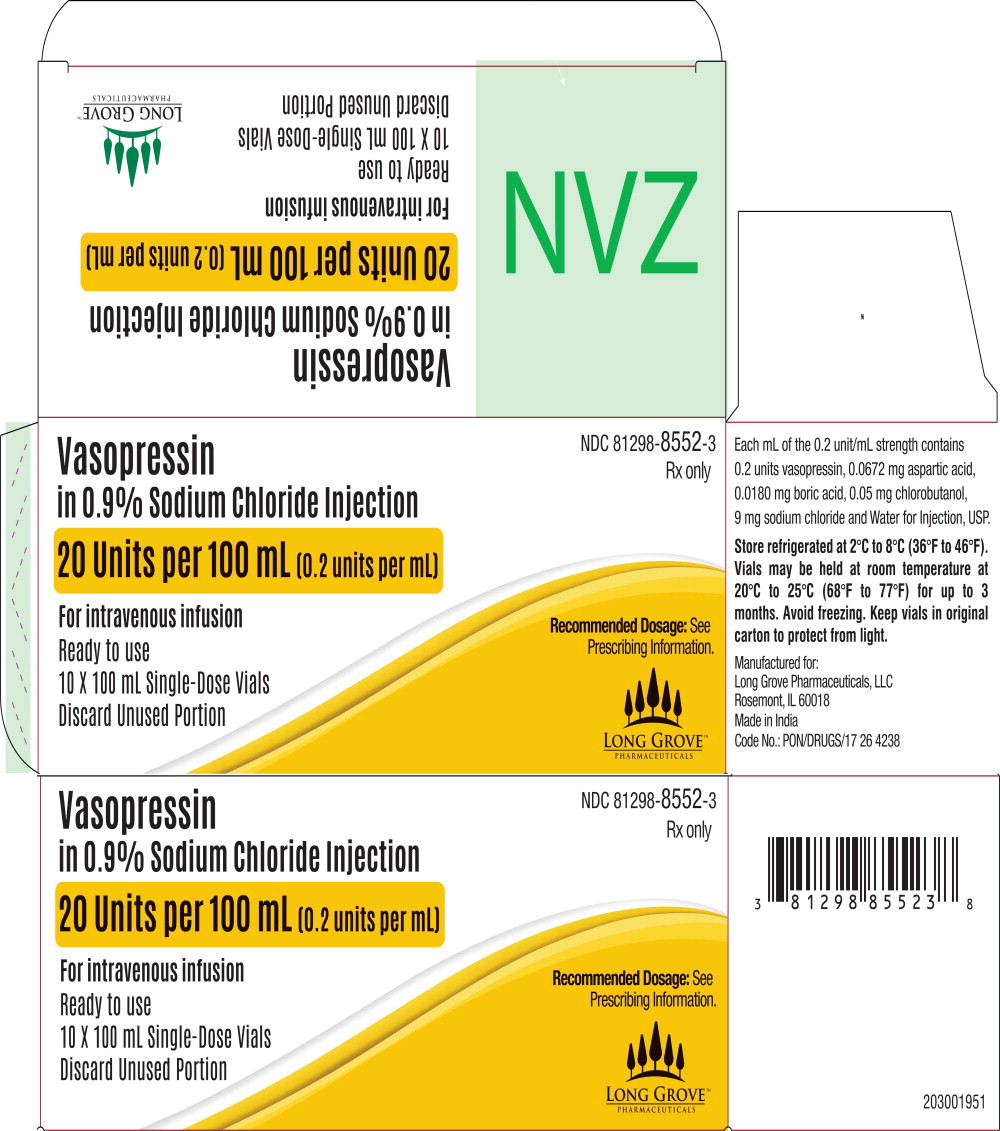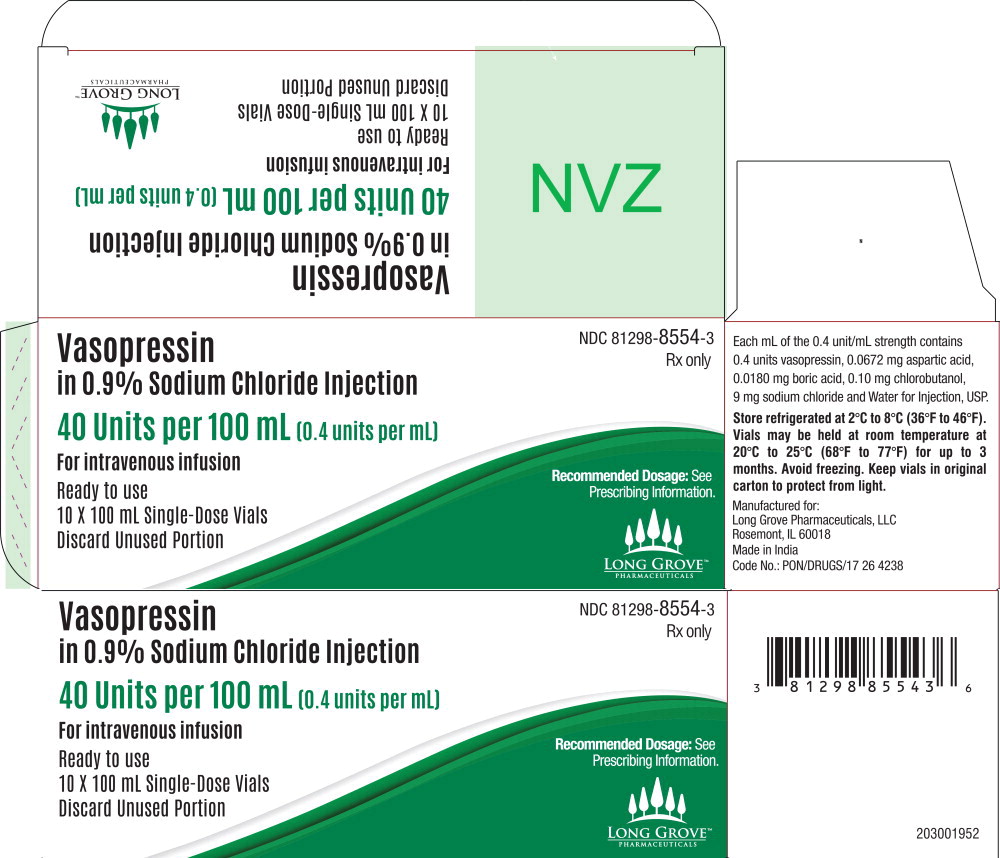 DRUG LABEL: Vasopressin in 0.9% Sodium Chloride
NDC: 81298-8552 | Form: SOLUTION
Manufacturer: Long Grove Pharmaceuticals, LLC
Category: prescription | Type: HUMAN PRESCRIPTION DRUG LABEL
Date: 20250617

ACTIVE INGREDIENTS: VASOPRESSIN 0.2 [USP'U]/1 mL
INACTIVE INGREDIENTS: CHLOROBUTANOL 0.05 mg/1 mL; ASPARTIC ACID 0.0672 mg/1 mL; BORIC ACID 0.0180 mg/1 mL; SODIUM CHLORIDE 9 mg/1 mL; WATER

HIGHLIGHTS OF PRESCRIBING INFORMATION

These highlights do not include all the information needed to use VASOPRESSIN IN SODIUM CHLORIDE INJECTION safely and effectively. See full prescribing information for VASOPRESSIN IN SODIUM CHLORIDE INJECTION.
VASOPRESSIN injection, for intravenous use
Initial U.S. Approval: 2014

1 INDICATIONS AND USAGE

- Vasopressin in Sodium Chloride Injection is indicated to increase blood pressure in adults with vasodilatory shock who remain hypotensive despite fluids and catecholamines. (1)

2 DOSAGE AND ADMINISTRATION

- This product does not require further dilution prior to administration. (2.1)
- Post-cardiotomy shock: 0.03 units/minute to 0.1 units/minute by intravenous infusion (2.2)
- Septic shock: 0.01 units/minute to 0.07 units/minute by intravenous infusion (2.2)

3 DOSAGE FORMS AND STRENGTHS

Injection: in a premixed single-dose, ready to use vial. (3)

- 20 units/100 mL (0.2 units/mL) in 0.9% Sodium Chloride
- 40 units/100 mL (0.4 units/mL) in 0.9% Sodium Chloride
- 50 units/50 mL (1 unit/mL) in 0.9% Sodium Chloride

4 CONTRAINDICATIONS

- Vasopressin in Sodium Chloride Injection is contraindicated in patients with known allergy or hypersensitivity to 8-L-arginine vasopressin or chlorobutanol. (4)

5 WARNINGS AND PRECAUTIONS

- Can worsen cardiac function. (5.1)
- Reversible diabetes insipidus (5.2)

6 ADVERSE REACTIONS

The most common adverse reactions include decreased cardiac output, bradycardia, tachyarrhythmias, hyponatremia and ischemia (coronary, mesenteric, skin, digital). (6)

To report SUSPECTED ADVERSE REACTIONS, contact Long Grove Pharmaceuticals LLC at 1-855-642-2594 or FDA at 1-800-FDA-1088 or www.fda.gov/medwatch.

7 DRUG INTERACTIONS

- Pressor effects of catecholamines and Vasopressin in Sodium Chloride Injection are expected to be additive. (7.1)
- Indomethacin may prolong effects of Vasopressin in Sodium Chloride Injection. (7.2)
- Co-administration of ganglionic blockers or drugs causing SIADH may increase the pressor response. (7.3, 7.4)
- Co-administration of drugs causing diabetes insipidus may decrease the pressor response. (7.5)

8 USE IN SPECIFIC POPULATIONS

- Pregnancy: May induce uterine contractions. (8.1)
- Pediatric Use: Safety and effectiveness have not been established. (8.4)
- Geriatric Use: No safety issues have been identified in older patients. (8.5)

FULL PRESCRIBING INFORMATION

1 INDICATIONS AND USAGE

Vasopressin in Sodium Chloride Injection is indicated to increase blood pressure in adults with vasodilatory shock who remain hypotensive despite fluids and catecholamines.

2 DOSAGE AND ADMINISTRATION

2.1 Preparation of Solution

Inspect parenteral drug products for particulate matter and discoloration prior to use, whenever solution and container permit.

This product does not require further dilution prior to administration.

2.2 Administration

In general, titrate to the lowest dose compatible with a clinically acceptable response.

The recommended starting dose is:

Post-cardiotomy shock: 0.03 units/minute by intravenous infusion

Septic Shock: 0.01 units/minute by intravenous infusion

Titrate up by 0.005 units/minute at 10- to 15-minute intervals until the target blood pressure is reached. There are limited data for doses above 0.1 units/minute for postcardiotomy shock and 0.07 units/minute for septic shock. Adverse reactions are expected to increase with higher doses.

After target blood pressure has been maintained for 8 hours without the use of catecholamines, taper Vasopressin in Sodium Chloride Injection by 0.005 units/minute every hour as tolerated to maintain target blood pressure.

3 DOSAGE FORMS AND STRENGTHS

Vasopressin in Sodium Chloride Injection is a clear, colorless premixed solution for intravenous administration in a single-dose, ready to use vial available as:

- 20 units/100 mL (0.2 units/mL) in 0.9% Sodium Chloride
- 40 units/100 mL (0.4 units/mL) in 0.9% Sodium Chloride
- 50 units/50 mL (1 unit/mL) in 0.9% Sodium Chloride

4 CONTRAINDICATIONS

Vasopressin in Sodium Chloride Injection is contraindicated in patients with known allergy or hypersensitivity to 8-L-arginine vasopressin or chlorobutanol.

5 WARNINGS AND PRECAUTIONS

5.1 Worsening Cardiac Function

A decrease in cardiac index may be observed with the use of vasopressin.

5.2 Reversible Diabetes Insipidus

Patients may experience reversible diabetes insipidus, manifested by the development of polyuria, a dilute urine, and hypernatremia, after cessation of treatment with vasopressin. Monitor serum electrolytes, fluid status and urine output after vasopressin discontinuation. Some patients may require readministration of vasopressin or administration of desmopressin to correct fluid and electrolyte shifts.

6 ADVERSE REACTIONS

The following adverse reactions associated with the use of vasopressin were identified in the literature. Because these reactions are reported voluntarily from a population of uncertain size, it is not possible to estimate their frequency reliably or to establish a causal relationship to drug exposure.

Bleeding/lymphatic system disorders: Hemorrhagic shock, decreased platelets, intractable bleeding

Cardiac disorders: Right heart failure, atrial fibrillation, bradycardia, myocardial ischemia

Gastrointestinal disorders: Mesenteric ischemia

Hepatobiliary: Increased bilirubin levels

Renal/urinary disorders: Acute renal insufficiency

Vascular disorders: Distal limb ischemia

Metabolic: Hyponatremia

Skin: Ischemic lesions

Postmarketing Experience

Reversible diabetes insipidus [see Warnings and Precautions (5.2)]

7 DRUG INTERACTIONS

7.1 Catecholamines

Use with catecholamines is expected to result in an additive effect on mean arterial blood pressure and other hemodynamic parameters. Hemodynamic monitoring is recommended; adjust the dose of vasopressin as needed.

7.2 Indomethacin

Use with indomethacin may prolong the effect of Vasopressin in Sodium Chloride Injection on cardiac index and systemic vascular resistance. Hemodynamic monitoring is recommended; adjust the dose of vasopressin as needed [see Clinical Pharmacology (12.3)].

7.3 Ganglionic Blocking Agents

Use with ganglionic blocking agents may increase the effect of Vasopressin in Sodium Chloride Injection on mean arterial blood pressure. Hemodynamic monitoring is recommended; adjust the dose of vasopressin as needed [see Clinical Pharmacology (12.3)].

7.4 Drugs Suspected of Causing SIADH

Use with drugs suspected of causing SIADH (e.g., SSRIs, tricyclic antidepressants, haloperidol, chlorpropamide, enalapril, methyldopa, pentamidine, vincristine, cyclophosphamide, ifosfamide, felbamate) may increase the pressor effect in addition to the antidiuretic effect of Vasopressin in Sodium Chloride Injection. Hemodynamic monitoring is recommended; adjust the dose of vasopressin as needed.

7.5 Drugs Suspected of Causing Diabetes Insipidus

Use with drugs suspected of causing diabetes insipidus (e.g., demeclocycline, lithium, foscarnet, clozapine) may decrease the pressor effect in addition to the antidiuretic effect of Vasopressin in Sodium Chloride Injection. Hemodynamic monitoring is recommended; adjust the dose of vasopressin as needed.

8 USE IN SPECIFIC POPULATIONS

8.1 Pregnancy

Risk Summary

There are no available data on Vasopressin in Sodium Chloride Injection use in pregnant women to inform a drug associated risk of major birth defects, miscarriage, or adverse maternal or fetal outcomes. Animal reproduction studies have not been conducted.

Clinical Considerations

Dose adjustments during pregnancy and the postpartum period: Because of increased clearance of vasopressin in the second and third trimester, the dose of Vasopressin in Sodium Chloride Injection may need to be increased [see Dosage and Administration (2.2) and Clinical Pharmacology (12.3)].

Maternal adverse reactions: Vasopressin in Sodium Chloride Injection may produce tonic uterine contractions that could threaten the continuation of pregnancy.

8.2 Lactation

There are no data on the presence of Vasopressin in Sodium Chloride Injection in either human or animal milk, the effects on the breastfed infant, or the effects on milk production.

8.4 Pediatric Use

Safety and effectiveness of Vasopressin in Sodium Chloride Injection in pediatric patients with vasodilatory shock have not been established.

8.5 Geriatric Use

Clinical studies of vasopressin did not include sufficient numbers of subjects aged 65 and over to determine whether they respond differently from younger subjects. Other reported clinical experience has not identified differences in responses between the elderly and younger patients. In general, dose selection for an elderly patient should be cautious, usually starting at the low end of the dosing range, reflecting the greater frequency of decreased hepatic, renal, or cardiac function, and of concomitant disease or other drug therapy [see Warnings and Precautions (5), Adverse Reactions (6), and Clinical Pharmacology (12.3)].

10 OVERDOSAGE

Overdosage with Vasopressin in Sodium Chloride Injection can be expected to manifest as consequences of vasoconstriction of various vascular beds (peripheral, mesenteric, and coronary) and as hyponatremia. In addition, overdosage may lead less commonly to ventricular tachyarrhythmias (including Torsade de Pointes), rhabdomyolysis, and non-specific gastrointestinal symptoms.

Direct effects will resolve within minutes of withdrawal of treatment.

11 DESCRIPTION

Vasopressin is a polypeptide hormone. Vasopressin in Sodium Chloride Injection is a sterile, aqueous solution of synthetic arginine vasopressin for intravenous administration.

Each mL of the 0.2 unit/mL strength contains 0.2 units vasopressin, 0.0672 mg aspartic acid, 0.0180 mg boric acid, 0.05 mg chlorobutanol, 9 mg sodium chloride and Water for Injection, USP. Each mL of the 0.4 unit/mL strength contains 0.4 units vasopressin, 0.0672 mg aspartic acid, 0.0180 mg boric acid, 0.10 mg chlorobutanol, 9 mg sodium chloride and Water for Injection, USP. Each mL of the 1 unit/mL strength contains 1 unit vasopressin, 0.0672 mg aspartic acid, 0.0180 mg boric acid, 0.25 mg chlorobutanol, 9 mg sodium chloride and Water for Injection, USP.

The chemical name of vasopressin is Cyclo (1-6) L-Cysteinyl-L-Tyrosyl-L-Phenylalanyl-L-Glutaminyl-
L-Asparaginyl-L-Cysteinyl-L-Prolyl-L-Arginyl-L-Glycinamide. It is a white to off-white amorphous powder, freely soluble in water. The structural formula is:

Molecular Formula: C46H65N15O12S2 Molecular Weight: 1084.23

12 CLINICAL PHARMACOLOGY

12.1 Mechanism of Action

Vasopressin causes vasoconstriction by binding to V1 receptors on vascular smooth muscle coupled to the Gq/11-phospholipase C-phosphatidyl-inositol-triphosphate pathway, resulting in the release of intracellular calcium. In addition, vasopressin stimulates antidiuresis via stimulation of V2 receptors which are coupled to adenyl cyclase.

12.2 Pharmacodynamics

At therapeutic doses exogenous vasopressin elicits a vasoconstrictive effect in most vascular beds including the splanchnic, renal, and cutaneous circulation. In addition, vasopressin at pressor doses triggers contractions of smooth muscles in the gastrointestinal tract mediated by muscular V1-receptors and release of prolactin and ACTH via V3 receptors. At lower concentrations typical for the antidiuretic hormone vasopressin inhibits water diuresis via renal V2 receptors. In addition, vasopressin has been demonstrated to cause vasodilation in numerous vascular beds that are mediated by V2, V3, oxytocin and purinergic P2 receptors.

In patients with vasodilatory shock vasopressin in therapeutic doses increases systemic vascular resistance and mean arterial blood pressure and reduces the dose requirements for norepinephrine. Vasopressin tends to decrease heart rate and cardiac output. The pressor effect is proportional to the infusion rate of exogenous vasopressin. The pressor effect reaches its peak within 15 minutes. After stopping the infusion the pressor effect fades within 20 minutes. There is no evidence for tachyphylaxis or tolerance to the pressor effect of vasopressin in patients.

12.3 Pharmacokinetics

Vasopressin plasma concentrations increase linearly with increasing infusion rates from 10 micro-units/kg/min to 200 micro-units /kg/min. Steady state plasma concentrations are achieved after 30 minutes of continuous intravenous infusion.

Distribution

Vasopressin does not appear to bind plasma protein. The volume of distribution is 140 mL/kg.

Elimination

At infusion rates used in vasodilatory shock (0.01 units/minute to 0.1 units/minute), the clearance of vasopressin is 9 to 25 mL/min/kg in patients with vasodilatory shock. The apparent t1/2 of vasopressin at these levels is ≤10 minutes.

Metabolism

Serine protease, carboxipeptidase and disulfide oxido-reductase cleave vasopressin at sites relevant for the pharmacological activity of the hormone. Thus, the generated metabolites are not expected to retain important pharmacological activity.

Excretion

Vasopressin is predominantly metabolized and only about 6% of the dose is excreted unchanged into urine.

Specific Populations

Pregnancy: Because of a spillover into blood of placental vasopressinase, the clearance of exogenous and endogenous vasopressin increases gradually over the course of a pregnancy. During the first trimester of pregnancy, the clearance is only slightly increased. However, by the third trimester the clearance of vasopressin is increased about 4-fold and at term up to 5-fold. After delivery, the clearance of vasopressin returns to preconception baseline within two weeks.

Drug Interactions

Indomethacin more than doubles the time to offset for vasopressin's effect on peripheral vascular resistance and cardiac output in healthy subjects [see Drug Interactions (7.2)].

The ganglionic blocking agent tetra-ethylammonium increases the pressor effect of vasopressin by 20% in healthy subjects [see Drug Interactions (7.3)].

Halothane, morphine, fentanyl, alfentanyl and sufentanyl do not impact exposure to endogenous vasopressin.

13 NONCLINICAL TOXICOLOGY

13.1 Carcinogenesis, Mutagenesis, Impairment of Fertility

No formal carcinogenicity or fertility studies with vasopressin have been conducted in animals. Vasopressin was found to be negative in the in vitro bacterial mutagenicity (Ames) test and the in vitro Chinese hamster ovary (CHO) cell chromosome aberration test. In mice, vasopressin has been reported to have an effect on function and fertilizing ability of spermatozoa.

14 CLINICAL STUDIES

Increases in systolic and mean blood pressure following administration of vasopressin were observed in 7 studies in septic shock and 8 in post-cardiotomy vasodilatory shock.

16 HOW SUPPLIED/STORAGE AND HANDLING

Vasopressin in Sodium Chloride Injection is a clear, colorless solution for intravenous administration available as:

NDC 81298-8552-3: A carton of 10 single dose vials. Each vial contains vasopressin 20 units/100 mL (0.2 units/mL).

NDC 81298-8554-3: A carton of 10 single dose vials. Each vial contains vasopressin 40 units/100 mL (0.4 units/mL).

NDC 81298-8550-3: A carton of 10 single dose vials. Each vial contains vasopressin 50 units/50 mL (1 unit/mL).

Store unopened vials refrigerated at 2°C to 8°C (36°F to 46°F). Do not freeze. Keep vials in original carton to protect from light.

Vials may be held up to three (3) months upon removal from refrigeration to room temperature storage conditions (20°C to 25°C [68°F to 77°F], USP Controlled Room Temperature), anytime within the labeled shelf life. Once removed from refrigeration, unopened vial should be marked to indicate the revised three (3) months expiration date. If the manufacturer's original expiration date is shorter than the revised expiration date, then the shorter date must be used. Do not use Vasopressin in Sodium Chloride Injection beyond the manufacturer's expiration date stamped on the vial.

Manufactured for:
Long Grove Pharmaceuticals, LLC
Rosemont, IL 60018

Made in India

PACKAGE LABEL

Principal Display Panel – 20 Units per 100 mL Carton Label

Vasopressin
in 0.9% Sodium Chloride Injection

20 Units per 100 mL (0.2 units per mL)

For intravenous infusion

Ready to use
10 x 100 mL Single-Dose Vials
Discard Unused Portion

NDC 81298-8552-3

Rx only

Recommended Dosage: See
Prescribing Information.

LONG GROVE™
PHARMACEUTICALS

PACKAGE LABEL

Principal Display Panel – 40 Units per 100 mL Carton Label

Vasopressin
in 0.9% Sodium Chloride Injection

40 Units per 100 mL (0.4 units per mL)

For intravenous infusion

Ready to use
10 x 100 mL Single-Dose Vials
Discard Unused Portion

NDC 81298-8554-3

Rx only

Recommended Dosage: See
Prescribing Information.

LONG GROVE™
PHARMACEUTICALS